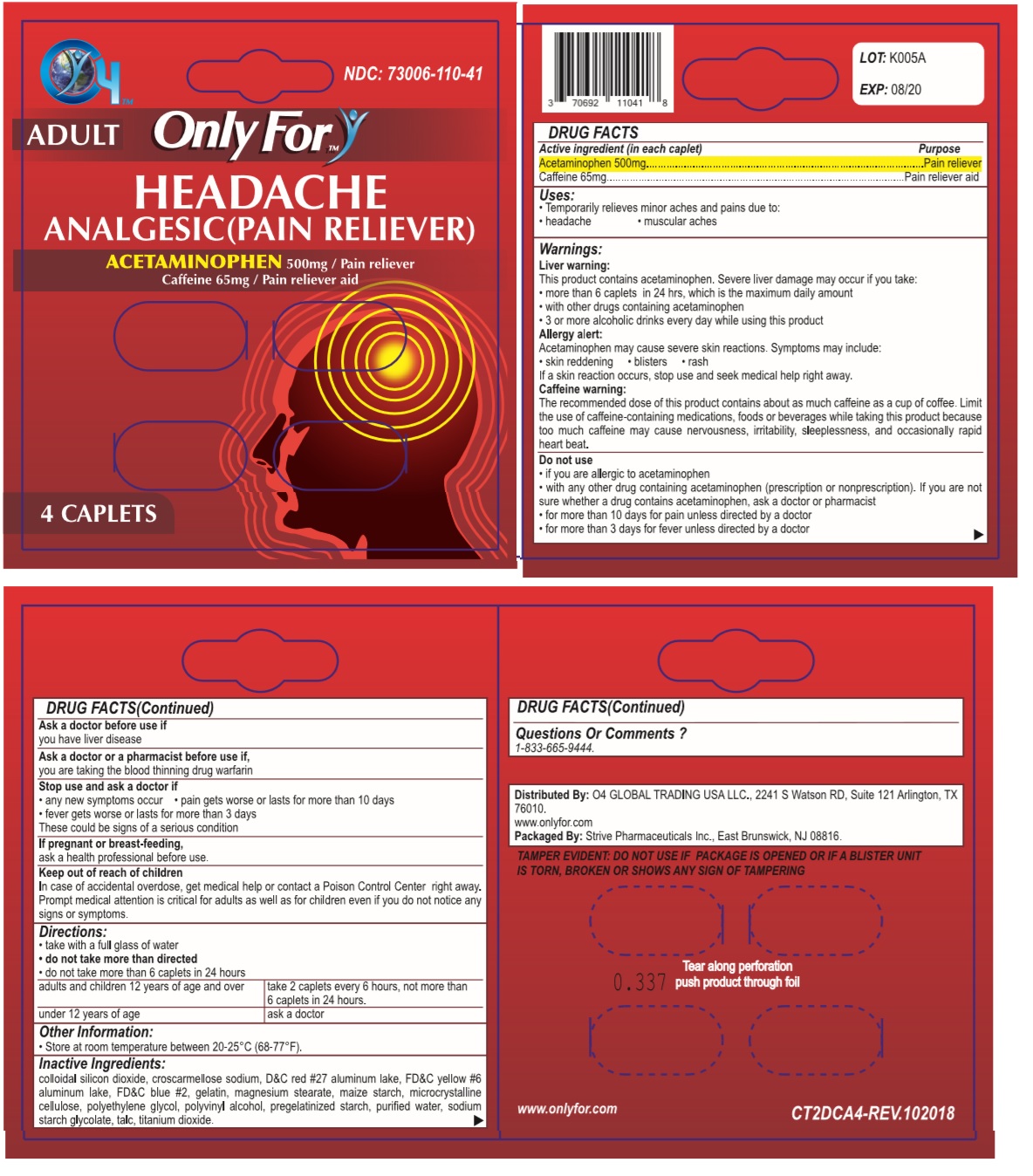 DRUG LABEL: Only For
NDC: 73006-110 | Form: TABLET
Manufacturer: O4 Global Trading Usa, Llc 
Category: otc | Type: HUMAN OTC DRUG LABEL
Date: 20190509

ACTIVE INGREDIENTS: ACETAMINOPHEN 500 mg/1 1; CAFFEINE 65 mg/1 1
INACTIVE INGREDIENTS: SILICON DIOXIDE; CROSCARMELLOSE SODIUM; D&C RED NO. 27 ALUMINUM LAKE ; FD&C YELLOW NO. 6; FD&C BLUE NO. 2; GELATIN, UNSPECIFIED; MAGNESIUM PALMITOSTEARATE; STARCH, CORN; MICROCRYSTALLINE CELLULOSE 101; POLYETHYLENE GLYCOL 400; POLYVINYL ALCOHOL (94000 MW); WATER; SODIUM STARCH GLYCOLATE TYPE A POTATO; TALC; TITANIUM DIOXIDE

Only For - HEADACHE

Active ingredient (in each caplet)

Acetaminophen 500mg

Caffeine 65mg

Purpose

Pain reliever

Pain reliever aid

Uses:

- Temporarily relieves minor aches and pains due to:
- headache • muscular aches

Warnings:

Liver warning:

This product contains acetaminophen. Severe liver damage may occur if you take:

- more than 6 caplets in 24 hours, which is the maximum daily amount
- with other drugs containing acetaminophen
- 3 or more alcoholic drinks every day while using this product

Allergy alert:

Acetaminophen may cause severe skin reactions. Symptoms may include:

• skin reddening • blisters • rash

If a skin reaction occurs, stop use and seek medical help right away.

Caffeine warning:

The recommended dose of this product contains about as much caffeine as a cup of coffee. Limit the use of caffeine-containing medications, foods or beverages while taking this product because too much caffeine may cause nervousness, irritability, sleeplessness, and occasionally rapid heart beat.

Do not use

- if you are allergic to acetaminophen
- with any other drug containing acetaminophen (prescription or nonprescription). If you are not sure whether a drug contains acetaminophen, ask a doctor or pharmacist
- for more than 10 days for pain unless directed by a doctor
- for more than 3 days for fever unless directed by a doctor

Ask a doctor before use if

you have liver disease

Ask a doctor or pharmacist before use if,

you are taking the blood thinning drug warfarin

Stop use and ask a doctor if

• any new symptoms occur • pain gets worse or lasts for more than 10 days

• fever gets worse or lasts for more than 3 days

These could be signs of a serious condition

If pregnant or breast-feeding,

ask a health professional before use.

Keep out of reach of childern

In case of accidental overdose, get medical help or contact a Poison Control Center right away. Prompt medical attention is critical for adults as well as for children even if you do not notice any signs or symptoms.

Directions:

- take with a full glass of water
- do not take more than directed
- do not take more than 6 caplets in 24 hours

adults and children 12 years of age and over | take 2 caplets every 6 hours, not more than 6 caplets in 24 hours.
under 12 years of age | ask a doctor

Other Information:

- Store at room temperature between 20-25°C (68-77°F).

Inactive Ingredients:

colloidal silicon dioxide, croscarmellose sodium, D&C red #27 aluminum lake, FD&C yellow #6 aluminum lake, gelatin, magnesium stearate, maize starch, microcrystalline cellulose, polyethylene glycol, polyvinyl alcohol, pregelatinized starch, purified water, sodium starch glycolate, talc, titanium dioxide.

Questions Or Comments ?

1-833-665-9444.

NDC: 73006-110-41

ADULT

ANALGESIC(PAIN RELIEVER)

Distributed By: O4 GLOBAL TRADING USA LLC., 2241 S Watson RD, Suite 121 Arlington, TX 76010.

www.onlyfor.com

Packaged By: Strive Pharmaceuticals Inc., East Brunswick, NJ 08816.

TAMPER EVIDENT: DO NOT USE IF PACKAGE IS OPENED OR IF A BLISTER UNIT IS TORN, BROKEN OR SHOWS ANY SIGN OF TAMPERING.

Tear along perforation push product through foil